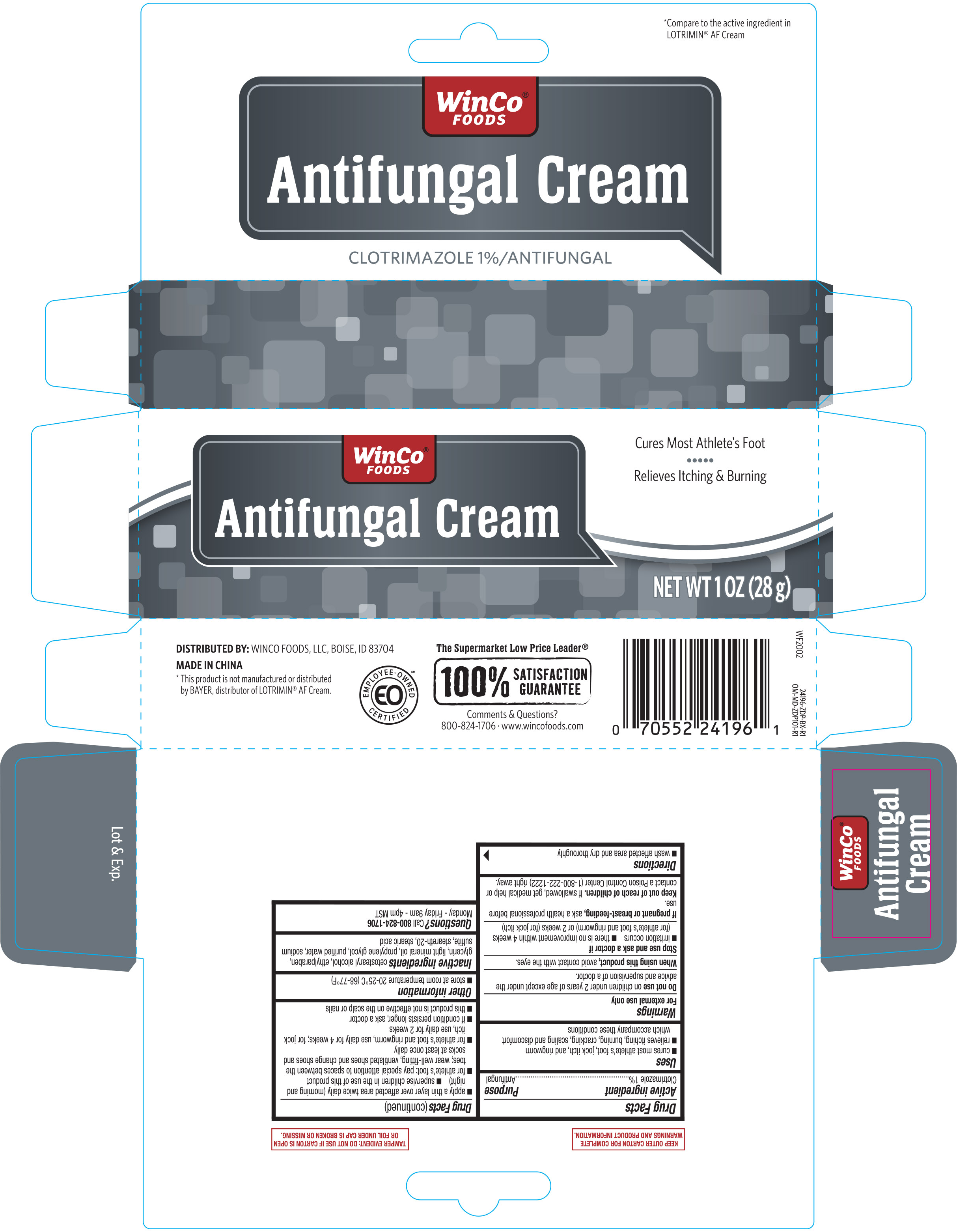 DRUG LABEL: WinCo Foods Antifungal
NDC: 67091-196 | Form: CREAM
Manufacturer: Winco Foods LLC
Category: otc | Type: HUMAN OTC DRUG LABEL
Date: 20251028

ACTIVE INGREDIENTS: CLOTRIMAZOLE 10 mg/1 g
INACTIVE INGREDIENTS: SODIUM SULFITE; ETHYLPARABEN; STEARETH-20; STEARIC ACID; CETOSTEARYL ALCOHOL; GLYCERIN; PROPYLENE GLYCOL; LIGHT MINERAL OIL; WATER

Winco Antifungal Clotrimazole Cream 1 oz 24196 ZDP 2021

Active ingredient Purpose

Clotrimazole 1%..............................Antifungal

Uses

- cures most athlete's foot, jock itch, and ringworm
- relieves itching, burning, cracking, scaling and discomfort which accompany these conditions

Warnings

For external use only

Do not use on children under 2 years of age except under the advice and supervision of a doctor.

When using this product, avoid contact with the eyes.

Stop use and ask a doctor if

- irritation occurs
- there is no improvement within 4 weeks (for athlete's foot and ringworm) or 2 weeks (for jock itch)

PREGNANCY OR BREAST FEEDING

If pregnant or breast-feeding, ask a health professional before use.

Keep out of reach of children. If swallowed, get medical help or contact a Poison Control Center (1-800-222-1222) right away.

Directions

- wash affected area and dry thoroughly
- apply a thin layer over affected area twice daily (morning and night)
- supervise children in the use of this product
- for athlete's foot: pay special attention to spaces between the toes; wear well-fitting, ventilated shoes and change socks at least once daily
- for athlete's foot and ringworm, use daily for 4 weeks; for jock itch, use daily for 2 weeks
- if condition persists longer, ask a doctor
- this product is not effective on the scalp or nails

Other information

- store at room temperature 20-25°C (68-77°F)

Inactive ignredients

cetostearly alcohol, ethylparaben, glycerin, light mineral oil, propylene glycol, purified water, sodium sulfite, steareth-20, stearic acid

Inactive ingredients

cetostearyl alchol, ethylparaben, glycerin, light mineral oil, propylene glycol, purified water, sodium sulfite, steareth-20, stearic acid

DOSAGE AND ADMINISTRATION

Distributed by:

Winco Foods, LLC

Boise, ID 83704

Made in China